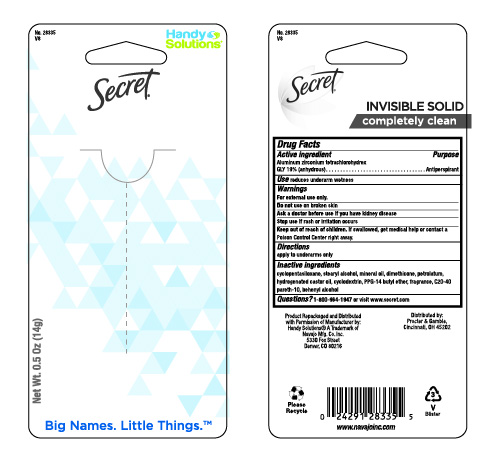 DRUG LABEL: Secret Outlast Completely Clean Invisible
NDC: 67751-220 | Form: STICK
Manufacturer: Navajo Manufacturing Company Inc.
Category: otc | Type: HUMAN OTC DRUG LABEL
Date: 20241003

ACTIVE INGREDIENTS: ALUMINUM ZIRCONIUM TETRACHLOROHYDREX GLY 19 g/100 g
INACTIVE INGREDIENTS: STEARYL ALCOHOL; MINERAL OIL; DIMETHICONE; KAOLIN; PETROLATUM; HYDROGENATED CASTOR OIL; PPG-14 BUTYL ETHER; C20-40 PARETH-10; DOCOSANOL; CYCLOMETHICONE 5; BETADEX

Secret Outlast Invisible Completely Clean

Drug Facts

Active ingredient

Aluminum zirconium tetrachlorohydrex Gly 19% (anhydrous)

Purpose

Antiperspirant

Use

reduces underarm wetness

Warnings

For external use only.

Do not use on broken skin

Ask a doctor before use if you have kidney disease

Stop use if rash or irritation occurs

Keep out of reach of children. If swallowed, get medical help or contact a Poison Control Center right away.

Directions

apply to underarms only

Inactive ingredients

Cyclopentasiloxane, stearyl alcohol, mineral oil, dimethicone, petrolatum, hydrogenated castor oil, kaolin, cyclodextrin, PPG-14 butyl ether, fragrance, C20-40 pareth-10, behenyl alcohol

Questions?

1-800-964-1947

Dist. by PROCTER & GAMBLE,
CINCINNATI, OH 45202.